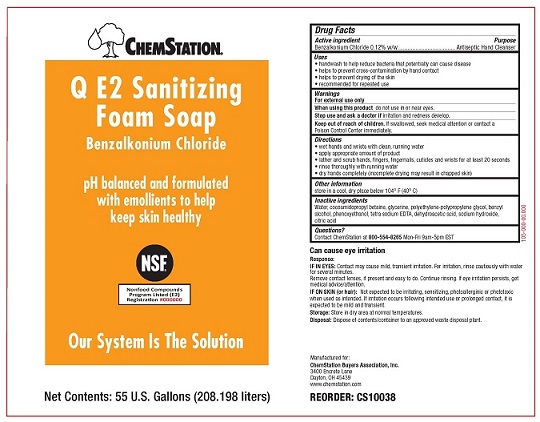 DRUG LABEL: Chemstation Q E2
NDC: 71212-102 | Form: LIQUID
Manufacturer: Chemstation
Category: otc | Type: HUMAN OTC DRUG LABEL
Date: 20250109

ACTIVE INGREDIENTS: BENZALKONIUM CHLORIDE 1.2 g/1 L
INACTIVE INGREDIENTS: CITRIC ACID MONOHYDRATE; SODIUM HYDROXIDE; WATER; GLYCERIN; COCAMIDOPROPYL BETAINE; POLYETHYLENE GLYCOL, UNSPECIFIED; BENZYL ALCOHOL; PHENOXYETHANOL; EDETIC ACID; DEHYDROACETIC ACID

ChemStation Q E2 Sanitizing Foam Soap

Drug Facts

Active Ingredient

Benzalkonium Chloride 0.12% w/w

Purpose

Antiseptic Hand Cleanser

Uses

- handwash to help reduce bacteria that potentially can cause disease
- helps to prevent cross contamination by hand contact
- helps to prevent drying of the skin
- recommended for repeated use

Warnings

For external use only

WHEN USING

When using this productdo not use in or near eyes.

Stop use and ask a doctor ifirritation and redness develop.

Keep out of reach of children.If swallowed, seek medical attention or contact a Poison Control Center immediately.

Directions

- wet hands and wrists with clean, running water
- apply appropriate amount of product
- lather and scrub hands, fingers, fingernails, cuticles and wrists for at least 20 seconds
- rinse thoroughly with running water
- dry hands completely (incomplete drying may result in chapped skin)

Other Information

store in a cool, dry place below 104° F (40° C)

Inactive Ingredients

Water, cocoamidopropy betaine, glycerine, polyethylene-polypropylene glycol, benzyl alcohol, phenoxyethanol, tetra sodium EDTA, dehydroacetic acid, sodium hydroxide, citric acid

Questions?

Contact ChemStation at 800-554-8265Mon-Fri 9am-5pm EST

OTHER SAFETY INFORMATION

Can cause eye irritation

Response:

IF IN EYES:Contact may cause mild, transient irritation. For irritation, rinse cautiously with water for several minutes.

Remove contact lenses, if present and easy to do. Continue rinsing. If eye irritation persists, get medical advice/attention.

IF ON SKIN (or hair):Not expected to be irritating, sensitizing, photoallerginic or phototoxic when used as intended. If irritation occurs following intended use or prolonged contact, it is expected to be mild and transient.

Storage:Store in a dry area at normal temperatures.

Disposal:Dispose of contents/container to an approved waste disposal plant.

Manufactured for:

ChemStation Buyers Association, Inc.

3400 Encrete Lane

Dayton, OH 45439

www.chemstation.com

PACKAGE LABEL

CHEMSTATION®

Q E2 Sanitizing Foam Soap

Benzalkonium Chloride

pH balanced and formulated with emollients to help keep skin healthy

Our System Is The Solution

Net Contents: 55 U.S.Gallons (208.198 liters)